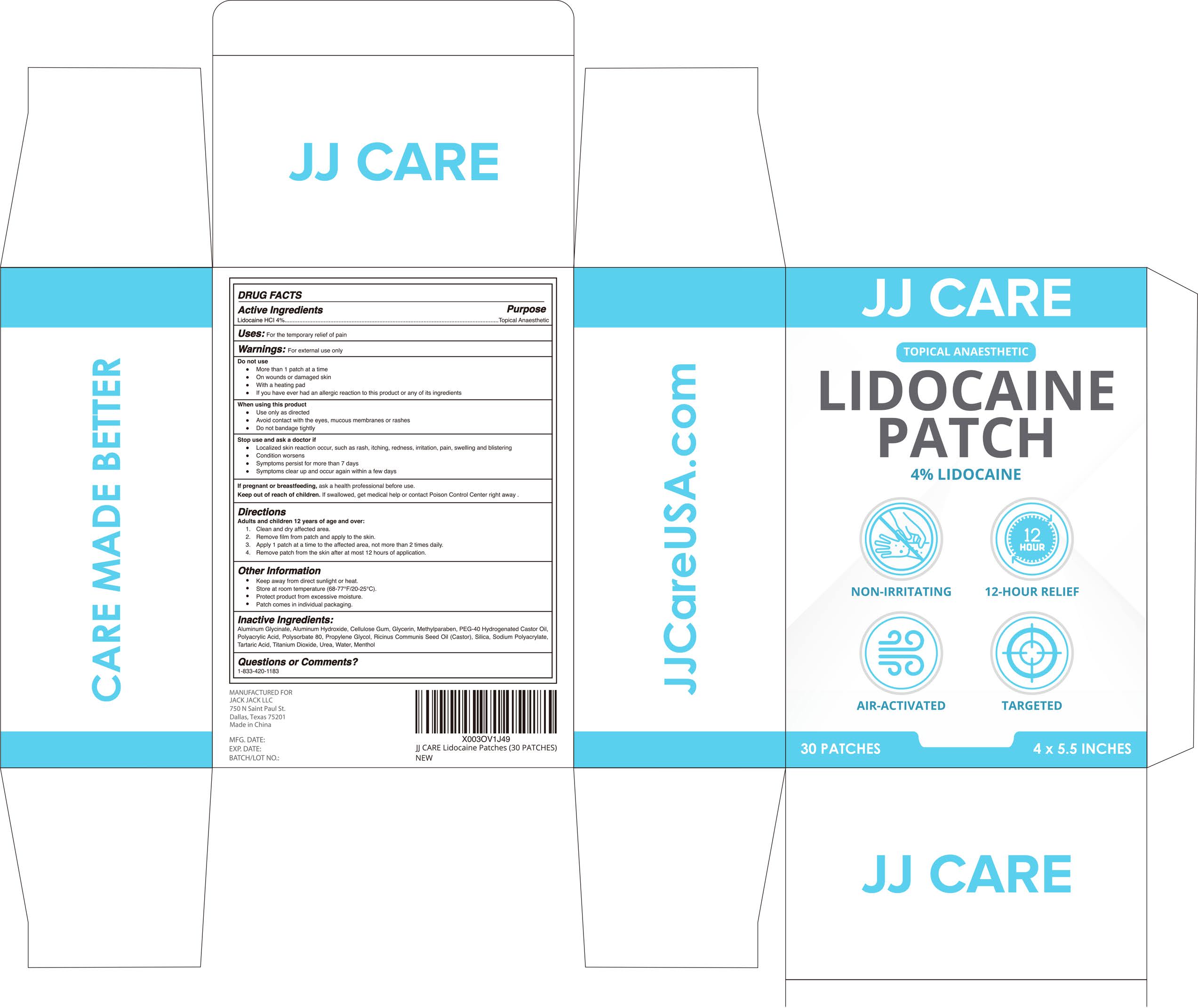 DRUG LABEL: Lidocaine Patch
NDC: 81484-501 | Form: PATCH
Manufacturer: Anhui Miao De Tang Pharmaceutical Co., Ltd.
Category: otc | Type: HUMAN OTC DRUG LABEL
Date: 20231114

ACTIVE INGREDIENTS: LIDOCAINE HYDROCHLORIDE 0.4 g/1 1
INACTIVE INGREDIENTS: ALUMINUM HYDROXIDE; GLYCERIN; POLYOXYL 40 HYDROGENATED CASTOR OIL; DIHYDROXYALUMINUM AMINOACETATE ANHYDROUS; POLYSORBATE 80; METHYLPARABEN; TARTARIC ACID; CARBOXYMETHYLCELLULOSE SODIUM (0.9 CARBOXYMETHYL SUBSTITUTION PER SACCHARIDE; 130 MPA.S AT 4%); POLYACRYLIC ACID (250000 MW); PROPYLENE GLYCOL; CASTOR OIL; SILICON DIOXIDE; UREA; WATER; SODIUM POLYACRYLATE (2500000 MW); TITANIUM DIOXIDE; RACEMENTHOL

LIDOCAINE PATCH

LIDOCAINE PATCH

ACTIVE INGREDIENT

Lidocaine HCI 4% Purpose:Topical Analgesic

PURPOSE

For the temporary relief of pain，LIDOCAINE PATCH

INDICATIONS AND USAGE

LIDOCAINE PATCH to help Temporarily relteves minor pain

WARNINGS

For external use only. Flammable.

DO NOT USE

More than 1 patch at a time
On wounds or damaged skin
With a heating pad
If you have ever had an allergic reaction to this product or any of its ingredients

WHEN USING

Use only as directed
Avoid contact with the eyes, mucous membranes or rashes

Do not bandage tightly

STOP USE

Localized skin reaction occur, such as rash, itching, redness, iritation, pain, swelling and blistering

Condition worsens
Symptoms persist for more than 7 days

Symptoms clear up and occur again within a few days

Keep out of reach of children. If swallowed, get medical help or contact a Poison Control Center right away.

DOSAGE AND ADMINISTRATION

Adults and children over 12 years:
·Wash and dry the affected areaRemove backing from patch by firmty grasping both ends and gently pulling until backing separates in the middle
· Carefully remove smaller portion of back,ng from patch and apply exposed portion of patch to aected areaOnce exposed portion of

· patch is pooned.carefully remove remaining backing tocomplelely apply patch to afected areaCarefully remove smaller portion of

· backing from patch and apply exposed portion of patch to affected area

· Use only 1 patch for a maximum of 24 hours

STORAGE AND HANDLING

· Keep away from direc sunlight or heat
· Store at room temperature (68-77F/20-25°C)
· Protect product from excessive moisture
· Patch comes in individual packaging

INACTIVE INGREDIENT

Aluminum Glycinate,Aluminum Hydroxide, Cellulose Gum, Glycerin, Methylparaben, PEG-40 Hydrogenated Castor Oil,Polyacrylic Acid,Polysorbate 80,Propylene Glycol, Ricinus Communis Seed Oil (Castor), Silica, Sodium Polyacrylate,Tartaric Acid,Titanium Dioxide,Urea,Water, Menthol